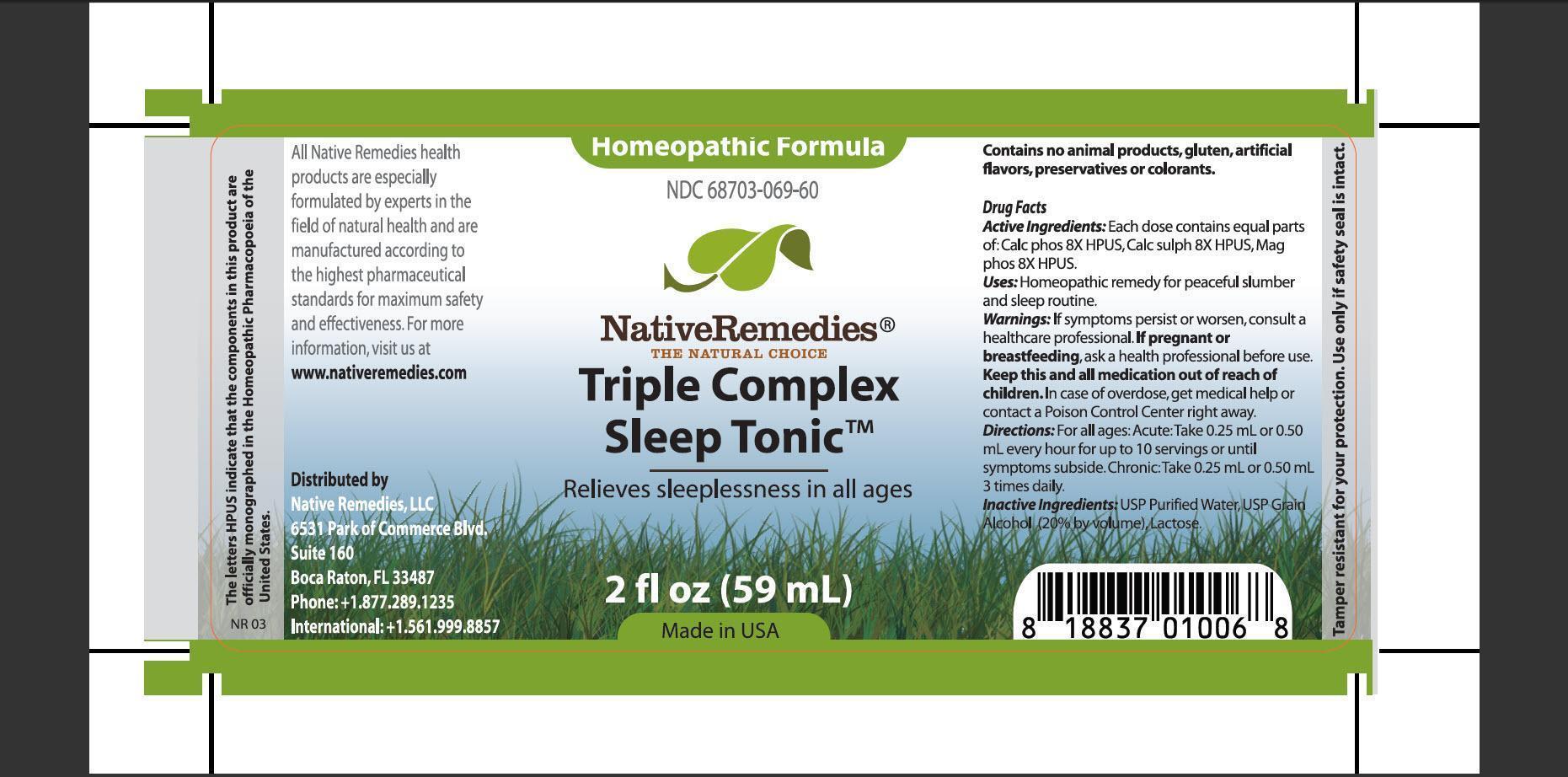 DRUG LABEL: Triple Complex Sleep Tonic
                
NDC: 68703-069 | Form: TINCTURE
Manufacturer: Native Remedies, LLC
Category: homeopathic | Type: HUMAN OTC DRUG LABEL
Date: 20130404

ACTIVE INGREDIENTS: TRIBASIC CALCIUM PHOSPHATE 8 [hp_X]/1 mL; CALCIUM SULFATE ANHYDROUS 8 [hp_X]/1 mL; MAGNESIUM PHOSPHATE, DIBASIC TRIHYDRATE 8 [hp_X]/1 mL
INACTIVE INGREDIENTS: WATER; ALCOHOL; LACTOSE

Triple Complex Sleep Tonic

PURPOSE

Relieves sleepless in all ages

ACTIVE INGREDIENT

Active Ingredients: Each dose contains equal parts of: Calc phos 8X HPUS, Calc sulph 8X HPUS, Mag phos 8X HPUS

INDICATIONS AND USAGE

Uses: Homeopathic remedy for peaceful slumber and sleep routine

WARNINGS

Warnings: If symptoms persist or worsen, consult a healthcare professional

PREGNANCY OR BREAST FEEDING

If pregnant or breastfeeding, ask a health professional before use

KEEP OUT OF REACH OF CHILDREN

Keep this and all medication out of reach of children

OVERDOSAGE

In case of overdose, get medical help or contact a Poison Control Center right away

DOSAGE AND ADMINISTRATION

Directions:For all ages: Acute: Take 0.25 mL or 0.50 mL every hour for up to 10 servings or until symptoms subside. Chronic: Take 0.25 mL or 0.50 mL 3 times daily

INACTIVE INGREDIENT

Inactive Ingredients: USP Purified Water, USP Grain Alcohol (20% by volume), Lactose

PATIENT COUNSELING INFORMATION

The letters HPUS indicate that the components in this product are officially monographed in the Homeopathic Pharmacopoeia of the United States.

All Native Remedies health products are especially formulated by experts in the field of natural health and are manufactured according to the highest pharmaceutical standards for maximum safety and effectiveness. For more information, visit us at www.nativeremedies.com

Distributed by
Native Remedies, LLC
6531 Park of Commerce Blvd.
Suite 160
Boca Raton, FL 33487
Phone: +1.877.289.1235
International: +1.561.999.8857

Contains no animal products, gluten, artificial flavors, preservatives or colorants

STORAGE AND HANDLING

Tamper resistant for your protection. Use only if safety seal is intact